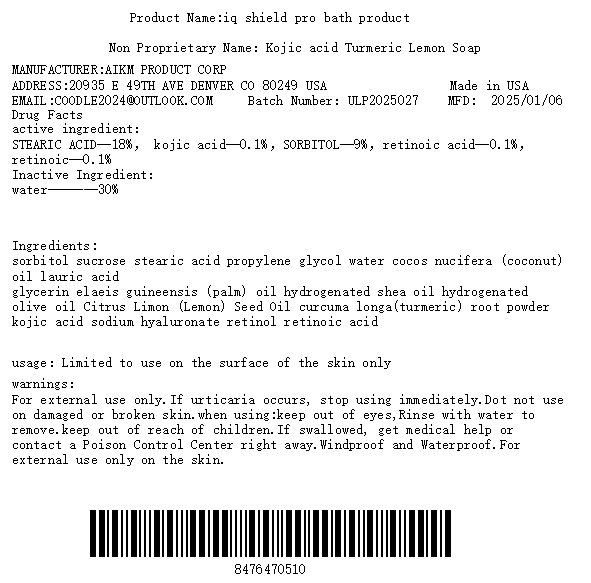 DRUG LABEL: turmeric kojic acid product
NDC: 84764-705 | Form: SOAP
Manufacturer: AIKM Product Corp
Category: otc | Type: HUMAN OTC DRUG LABEL
Date: 20250109

ACTIVE INGREDIENTS: RETINOL 10 mg/1 g; STEARIC ACID 180 mg/1 g; SORBITOL 90 mg/1 g; RETINOIC ACID 10 mg/1 g; KOJIC ACID 10 mg/1 g
INACTIVE INGREDIENTS: WATER 300 mg/1 g

active ingredient

STEARIC ACID 18%， kojic acid 0.1%，SORBITOL 9%，retinoic acid 0.1%，retinoic 0.1%

Purpose

wash bath

usage

Wash hands, take a shower, clean the skin,

warnings

For external use only

stop

rash occurs

do not use

on damaged or broken skin

when using

keep out of eyes. Rinse with water to remove.

keep out of reach of children

If swallowed, get medical help or contact a Poison Control Center right away.

storage

Windproof and Waterproof

INACTIVE INGREDIENT

INACTIVE INGREDIENT----water

DOSAGE

STEARIC ACID 18%， kojic acid 0.1%，SORBITOL 9%，retinoic acid 0.1%，retinoic 0.1%

Use the product according to the doctor's advice

RECENT MAJOR CHANGES

no